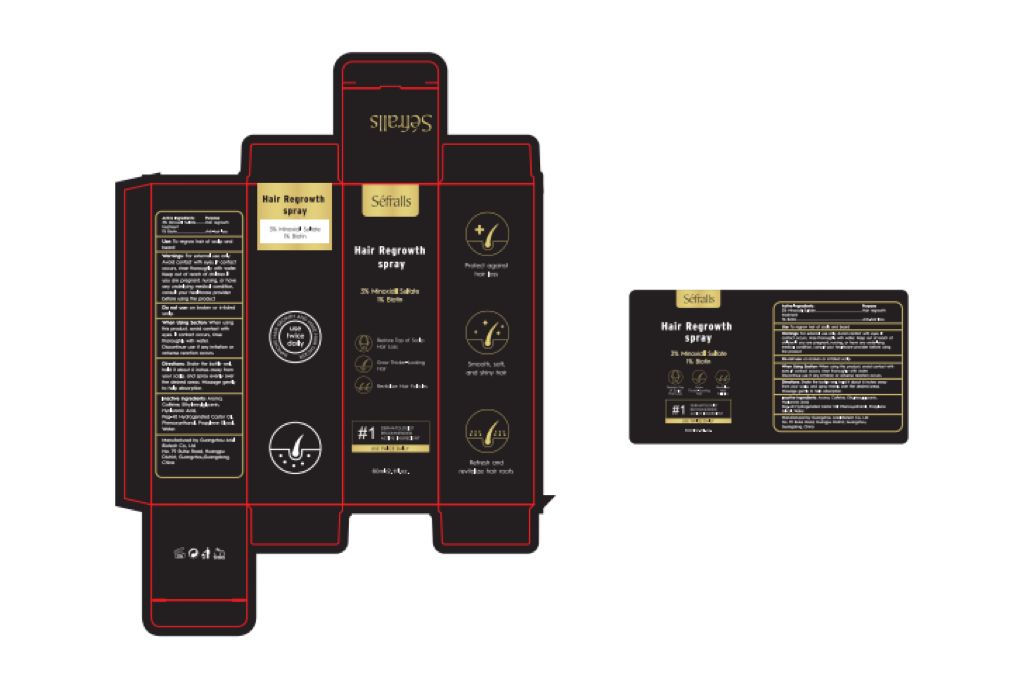 DRUG LABEL: Hair Regrowth
NDC: 84148-007 | Form: SPRAY
Manufacturer: Guangzhou Ariel Biotech Co., Ltd.
Category: otc | Type: HUMAN OTC DRUG LABEL
Date: 20240718

ACTIVE INGREDIENTS: BIOTIN 1 g/100 mL; MINOXIDIL SULFATE 3 g/100 mL
INACTIVE INGREDIENTS: AROMADENDRIN; CAFFEINE; ETHYLHEXYLGLYCERIN; HYALURONIC ACID; POLYOXYL 40 HYDROGENATED CASTOR OIL; PHENOXYETHANOL; PROPYLENE GLYCOL; WATER

84148-007

Active Ingredient(s)

Minoxidil Sulfate. 3%

BIOTIN 1%

Purpose

Hair regrowth treatment
Anti-hair loss

Use

Use: To regrow hair of scalp and beard

Warnings

Warnings: For external use only. Avoid contact with eyes. If contact occurs, rinse thoroughly with water.
Keep out of reach of children.If you are pregnant, nursing, or have any underlying medical condition,
consult your healthcare provider before using the product.

Do not use: on broken or irritated scalp.

WHEN USING

When Using Section: When using this product, avoid contact with eyes. If contact occurs, rinse
thoroughly with water. Discontinue use if any irritation or adverse reaction occurs.

STOP USE

●Chest pain, rapid heartbeat, faintness or dizziness occurs.
●Scalp iritation or redness occurs.

Keep out of reach of children.

Directions

Directions: Shake the bottle well, hold it about 6 inches away from your scalp, and spray evenly over
the desired areas. Massage gently to help absorption.

Other information

No Data

Inactive ingredients

Inactive ingredients: Aroma, Caffeine, Ethylhexylglycerin, Hyaluronic Acid, Peg-40 Hydrogenated Castor Oil,
Phenoxyethanol, Propylene Glycol, Water.